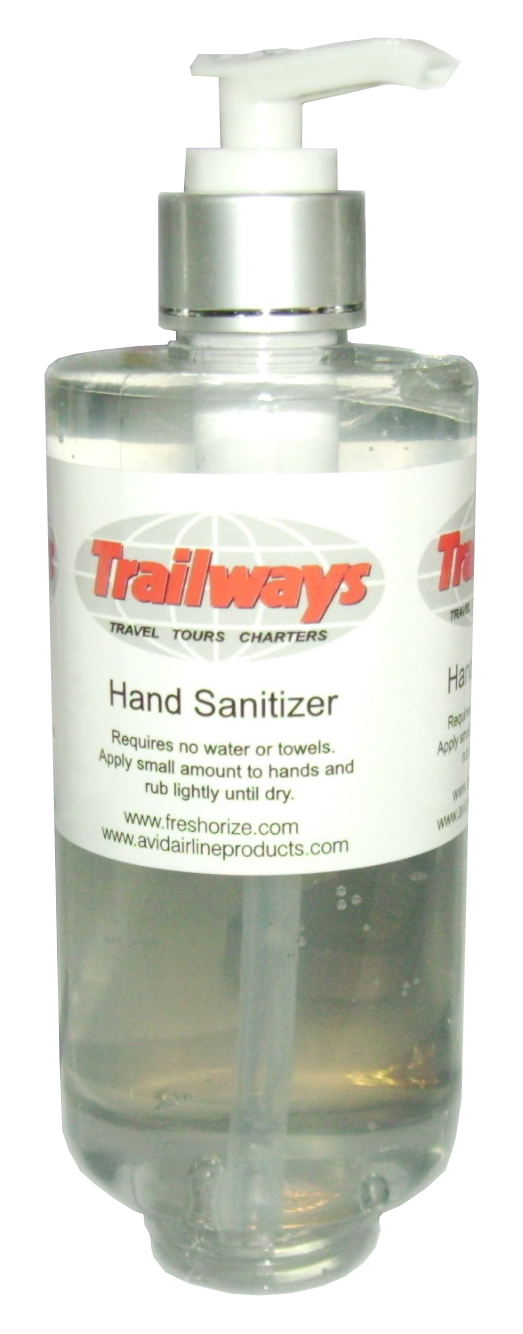 DRUG LABEL: Trailways
NDC: 52305-144 | Form: LOTION
Manufacturer: Freshorize, Ltd.
Category: otc | Type: HUMAN OTC DRUG LABEL
Date: 20100622

ACTIVE INGREDIENTS: Alcohol 250 mL/295 mL
INACTIVE INGREDIENTS: Water; ETHANOLAMINE

Drug Facts

Active Ingredient

Sanitizer. Topical hand sanitizer containing Isopropyl Alcohol that is a fast acting, broad spectrum and persistent antiseptic containing preparation that significantly reduces the number of microorganisms on the skin.

Use Information

Requires no water or towels. Apply small amount to hands and rub lightly until dry.

SAFE HANDLING WARNING

Safety: For External Use Only.
Do not use in Eyes. Avoid contact with eyes, should this occur rinse immediately with clean warm water.
Discontinue use if redness or swelling develops.
Flammable. Do not use near fire or flame.

Display of package label.

Picture of Package Label